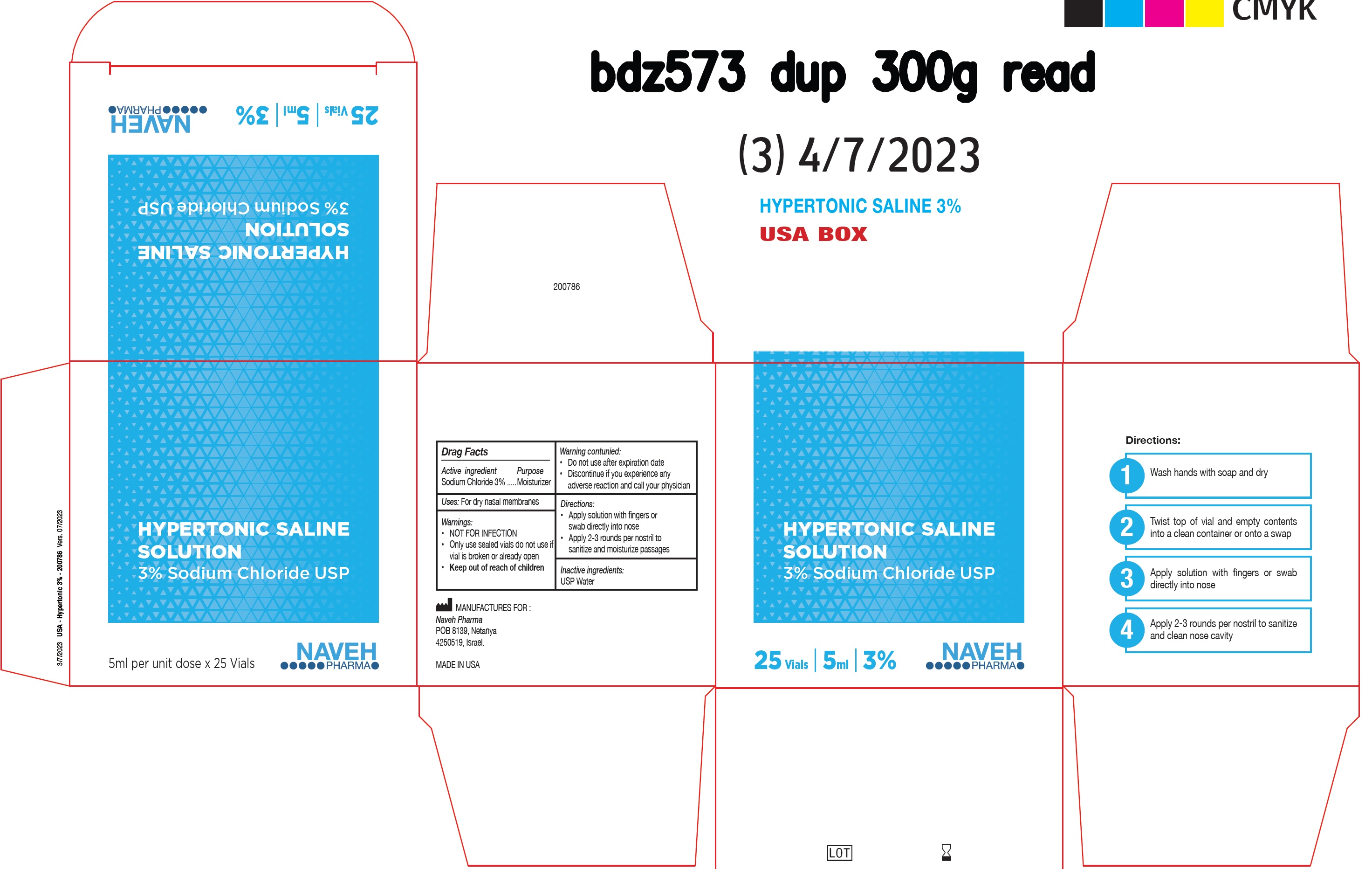 DRUG LABEL: Hypertonic Saline Solution Sodium Chloride
NDC: 85202-001 | Form: LIQUID
Manufacturer: NAVEH PHARMA (1996) LTD
Category: otc | Type: HUMAN OTC DRUG LABEL
Date: 20250212

ACTIVE INGREDIENTS: SODIUM CHLORIDE 30 mg/1 mL
INACTIVE INGREDIENTS: WATER

Hypertonic Saline Solution 3% Sodium Chloride USP

Active ingredient

Sodium Chloride 3%

Purpose

Moisturizer

Uses:

For dry nasal membranes

Wornings

- NOT FOR INFECTION
- Only use sealed vials do not use if vial is broken or already open

Do not use

- after expiration date
- Discontinue if you experience any adverse reaction and call your physician

Directions

- Apply solution with fingers or swab directly into nose
- Apply 2-3 rounds per nostril to sanitize and moisturize passages

Inactive ingredients:

USP Water